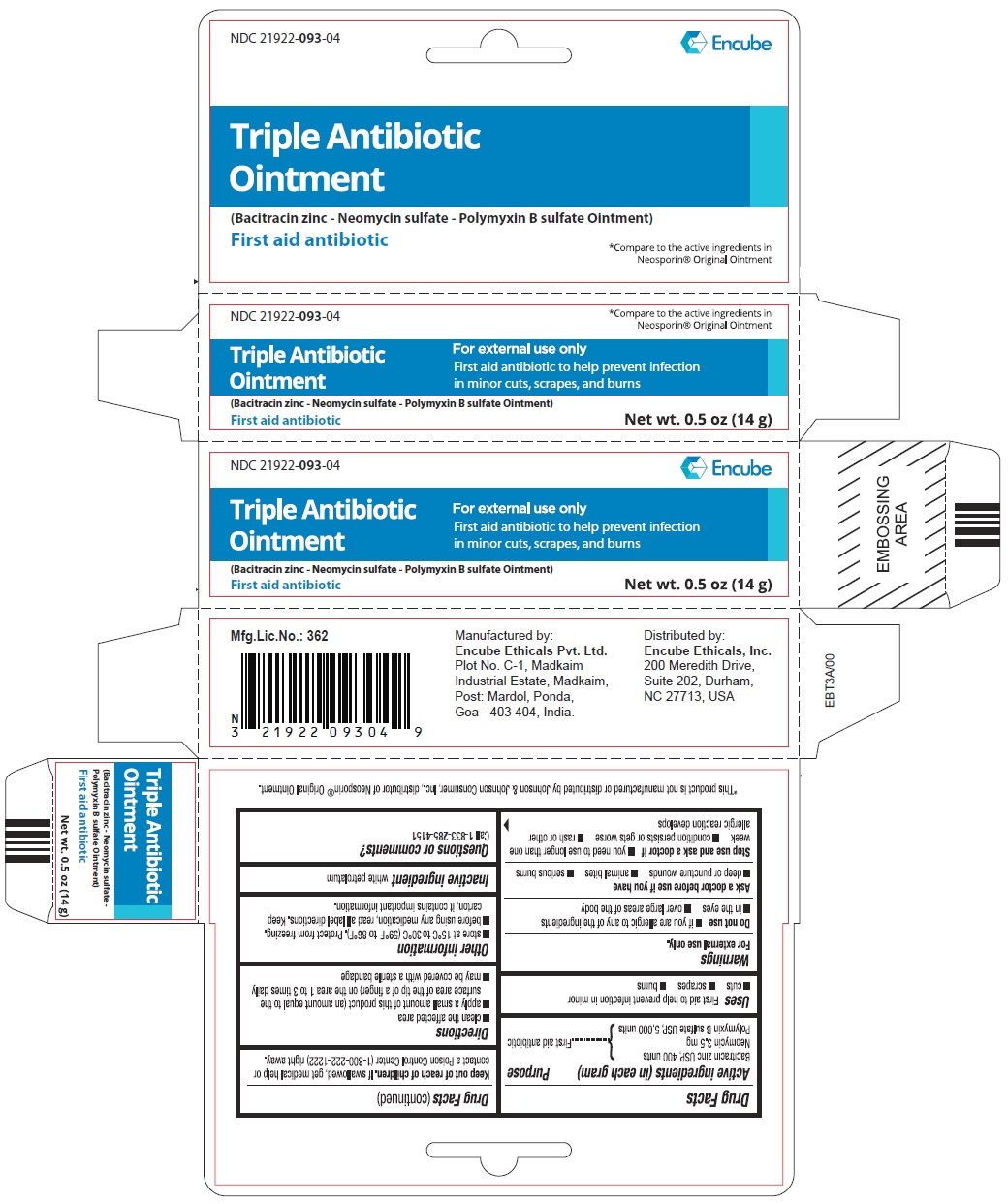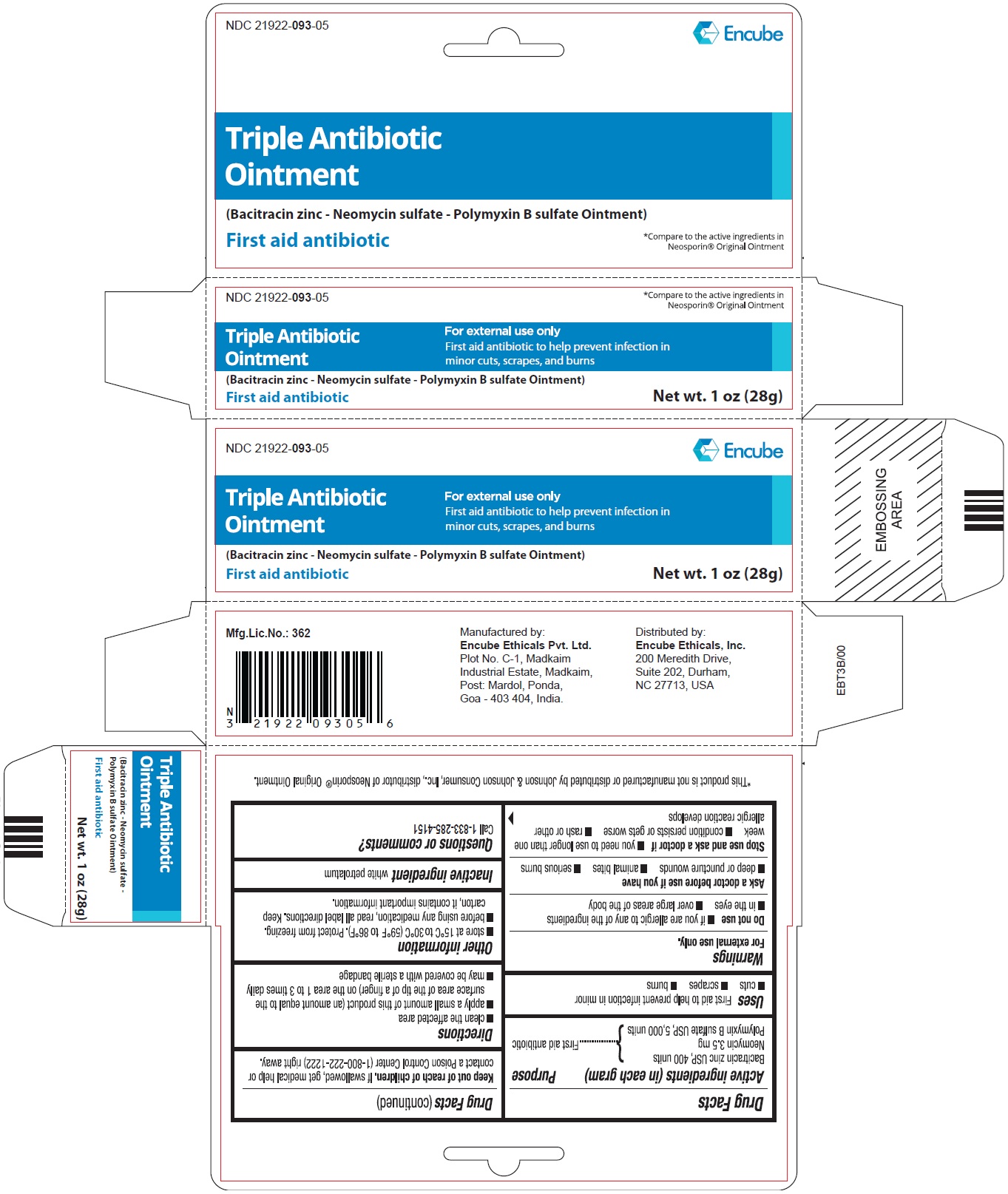 DRUG LABEL: TRIPLE ANTIBIOTIC
NDC: 21922-093 | Form: OINTMENT
Manufacturer: Encube Ethicals, Inc.
Category: otc | Type: HUMAN OTC DRUG LABEL
Date: 20250925

ACTIVE INGREDIENTS: BACITRACIN ZINC 400 [USP'U]/1 g; NEOMYCIN SULFATE 3.5 mg/1 g; POLYMYXIN B SULFATE 5000 [USP'U]/1 g
INACTIVE INGREDIENTS: WHITE PETROLATUM

Triple Antibiotic Ointment (Bacitracin Zinc - Neomycin Sulfate - Polymyxin B Sulfate)

Active ingredients (in each gram)

Bacitracin Zinc USP, 400 units

Neomycin 3.5 mg

Polymyxin B Sulfate USP, 5,000 units

Purpose

First aid antibiotic

Uses

First aid to help prevent infection in minor

- cuts

- scrapes
- burns

Warnings

For external use only.

Do not use

- if you are allergic to any of the ingredients
- in the eyes
- over large areas of the body

Ask a doctor before use if you have

■ deep or puncture wounds

■ animal bites

■ serious burns

Stop use and ask a doctor if

■ you need to use longer than one week

■ condition persists or gets worse

■ rash or other allergic reaction develops

Keep out of reach of children.

If swallowed, get medical help or contact a Poison Control Center (1-800-222-1222) right away.

Directions

■ clean the affected area
■ apply a small amount of this product (an amount equal to the surface area of the tip of a finger) on the area 1 to 3 times daily
■ may be covered with a sterile bandage

Other information

■ store at 15°C to 30°C (59°F to 86°F). Protect from freezing.

■ before using any medication, read all label directions. Keep carton, it contains important information.

Inactive ingredient

white petrolatum

Questions or comments?

Call 1-833-285-4151

PRINCIPAL DISPLAY PANEL

Triple Antibiotic Ointment

(Bacitracin zinc - Neomycin sulfate - Polymyxin B sulfate Ointment)

First aid antibiotic

NDC 21922-093-04

Net wt. 0.5 oz (14g)

Triple Antibiotic Ointment

(Bacitracin zinc - Neomycin sulfate - Polymyxin B sulfate Ointment)

First aid antibiotic

NDC 21922-093-05

Net wt. 1 oz (28g)